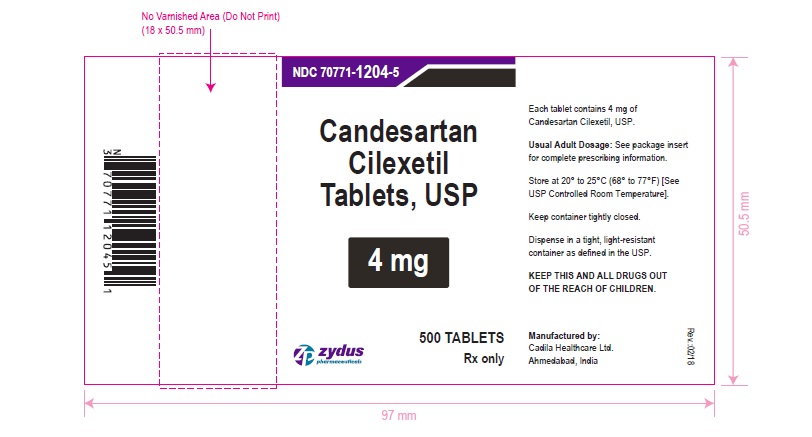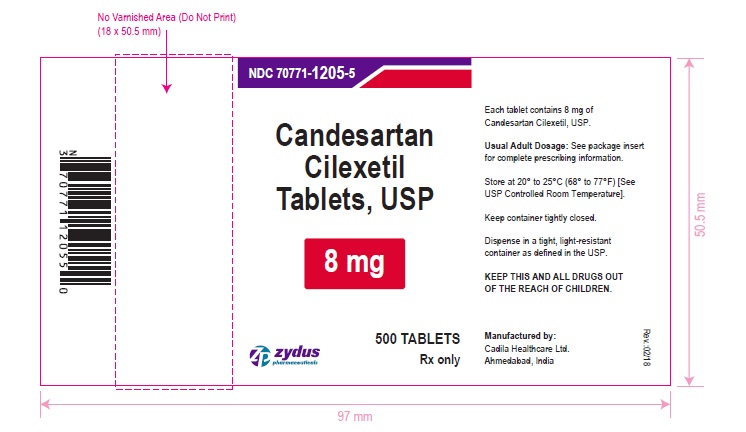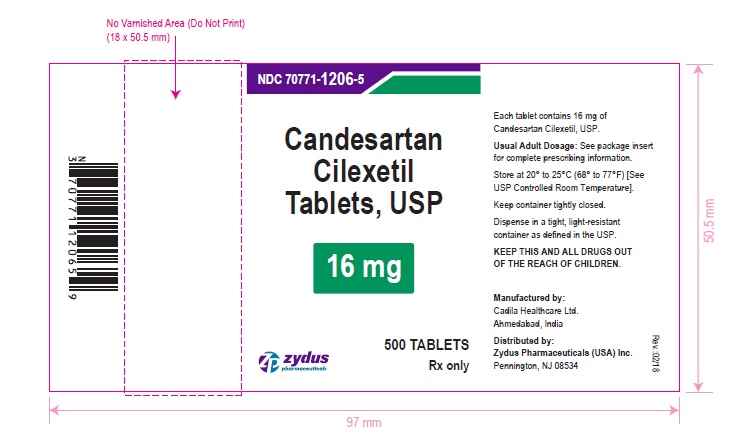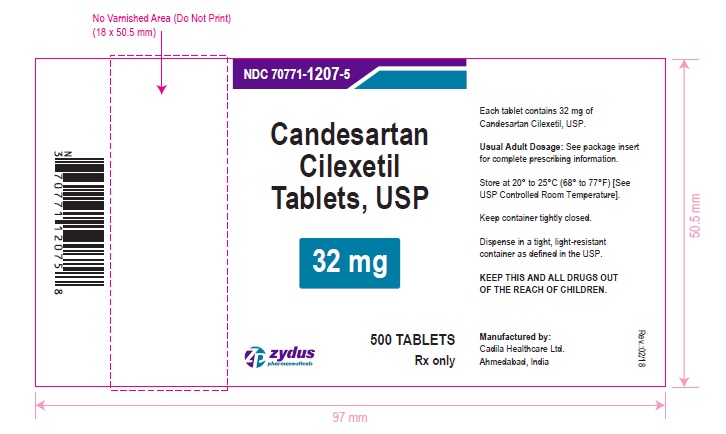 DRUG LABEL: Candesartan cilexetil
NDC: 70771-1204 | Form: TABLET
Manufacturer: Zydus Lifesciences Limited
Category: prescription | Type: HUMAN PRESCRIPTION DRUG LABEL
Date: 20251224

ACTIVE INGREDIENTS: CANDESARTAN CILEXETIL 4 mg/1 1
INACTIVE INGREDIENTS: CARBOXYMETHYLCELLULOSE CALCIUM; FERRIC OXIDE RED; HYDROXYPROPYL CELLULOSE (110000 WAMW); LACTOSE MONOHYDRATE; MAGNESIUM STEARATE; POLYETHYLENE GLYCOL 6000; STARCH, CORN

CANDESARTAN CILEXETIL TABLETS

PACKAGE LABEL.PRINCIPAL DISPLAY PANEL

NDC 70771-1204-5

Candesartan Cilexetil Tablets USP, 4 mg

Rx Only

500 tablets

NDC 70771-1205-5

Candesartan Cilexetil Tablets USP, 8 mg

Rx Only

500 tablets

NDC 70771-1206-5

Candesartan Cilexetil Tablets USP, 16 mg

Rx Only

500 tablets

NDC 70771-1207-5

Candesartan Cilexetil Tablets USP, 32 mg

Rx Only

500 tablets